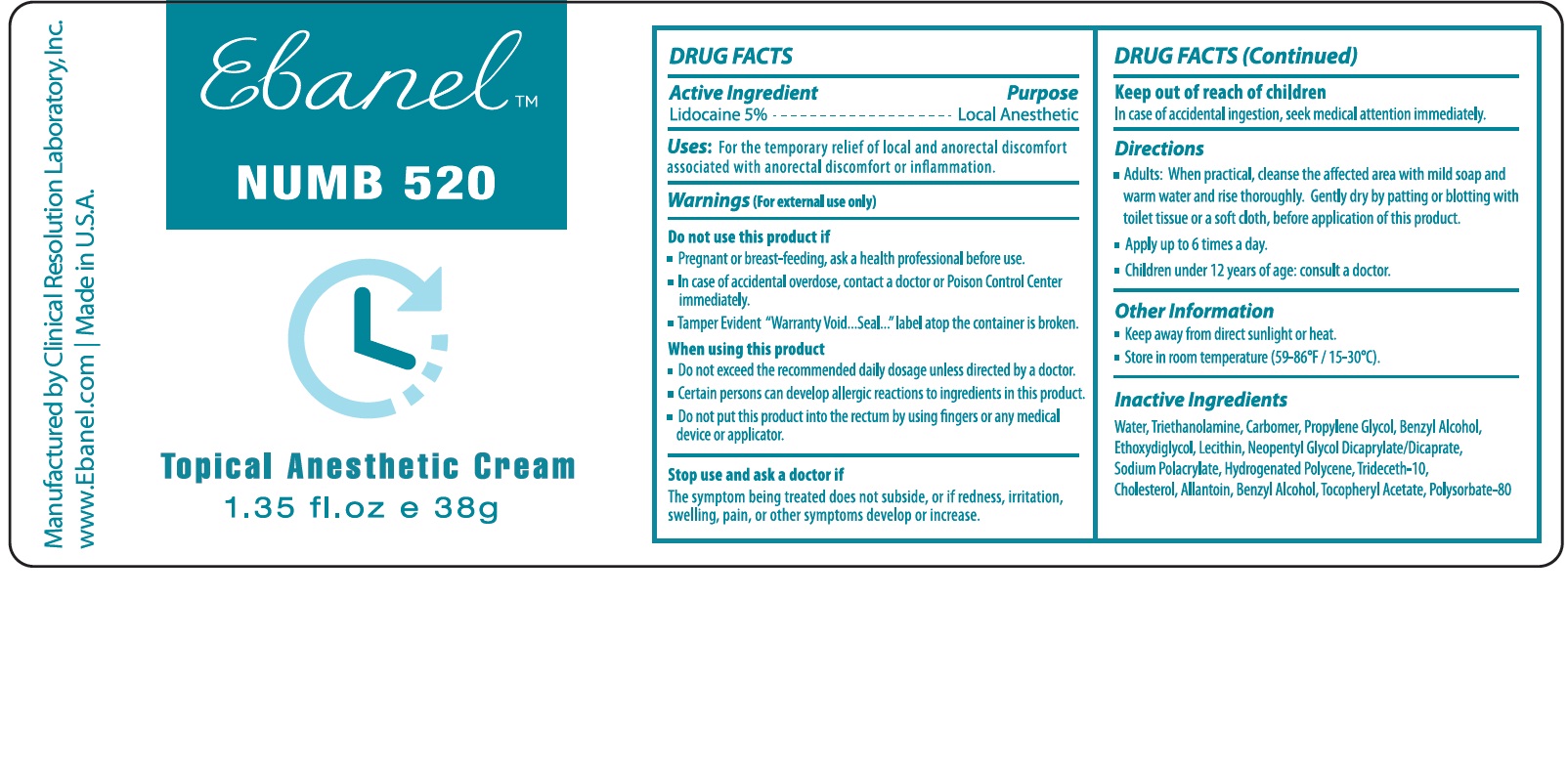 DRUG LABEL: Numb 520
NDC: 63742-002 | Form: CREAM
Manufacturer: Clinical Resolution Laboratory, Inc.
Category: otc | Type: HUMAN OTC DRUG LABEL
Date: 20231226

ACTIVE INGREDIENTS: LIDOCAINE 5 mg/1 g
INACTIVE INGREDIENTS: WATER; TROLAMINE; PROPYLENE GLYCOL; BENZYL ALCOHOL; DIETHYLENE GLYCOL MONOETHYL ETHER; NEOPENTYL GLYCOL DICAPRATE; TRIDECETH-10; CHOLESTEROL; ALLANTOIN; .ALPHA.-TOCOPHEROL ACETATE; POLYSORBATE 80

Numb 520

Active Ingredient

Lidocaine 5%

Purpose

Local Anesthetic

Uses

For the temporary relief of local and anorectal dicomfort associated with anorectal discomfort or inflammation.

Warnings

(For external use only)

Do not use this product if

- Pregnant or breast-feeding, ask a health professional before use.
- In case of accidental overdose, contact a doctor or Poison Control Center immediately.
- Tamper Evident "Warranty Void...Seal...label atop the container is broken."

When using this product

- Do not exceed the recommended daily dosage unless directed by a doctor.
- Certain persons can develop allergic reactions to ingredients in this product.
- Do not put this product into the rectum by using fingers or any medical device or applicator.

Stop use and ask a doctor if

The symptom being treated does not subside or if redness, irritation, swellinh, pain, or other symptoms develop or increase.

Keep out of reach of children

In case of accidental ingestion, seek medical attention immediately.

Directions

- Adults: When practical, cleanse the affected area with mild soap and warm water and rinse thoroughly. Gently dry by patting or blotting with toilet tissue or a soft cloth before application of this product.

- Apply up to 6 times a day.

- Children under 12 years of age: consult a doctor.

Other Information

- Keep away from direct sunlight or heat

- Store in room temperature (59-860F / 15-300C)

Inactive Ingredients

Water, Triethanolamine, Carbomer, Propylene Glycol, Benzyl Alcohol, Ehtoxydiglycol, Lecithin, Neopentyl Glycol Dicarprylate/Dicarpate, Sodiuym Polyacrylate, Hydrogenated Polydecene, Trideceth-10, Cholesterol, Allantoin, Benzyl Alcohol, Tocopherol Acetate, Polysorbate-80